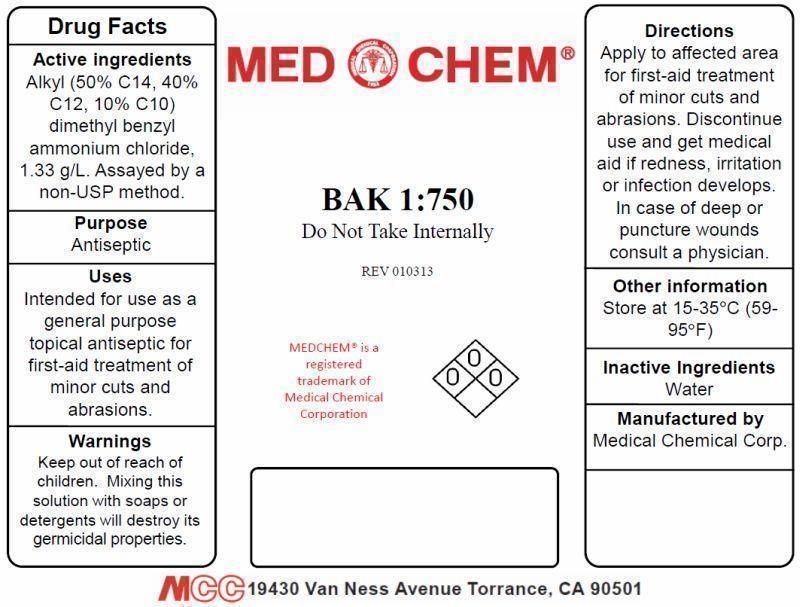 DRUG LABEL: BAK
NDC: 12745-145 | Form: LIQUID
Manufacturer: Medical Chemical Corporation
Category: otc | Type: HUMAN OTC DRUG LABEL
Date: 20250828

ACTIVE INGREDIENTS: BENZALKONIUM CHLORIDE 0.1713 g/100 mL
INACTIVE INGREDIENTS: WATER

BAK 1:750 Label

PURPOSE

Antiseptic

Active Ingredient: Alkyl (50% C14, 40% C12, 10% C10) dimethyl benzyl ammonium chloride, 1.33 g/l. Assayed by a non-USP method.

KEEP OUT OF REACH OF CHILDREN

Warnings: Keep out of reach of children. Mixing this solution with soaps or detergents will destroy its germicidal properties.

INDICATIONS AND USAGE

Uses: Intended for use as a general purpose topical antiseptic for first-aid treatment of minor cuts and abrasions.

WARNINGS

Caution: Mixing this solution with soaps or detergents will destroy its germicidal properties.

DOSAGE AND ADMINISTRATION

Usage: Apply to affected area for first-aid treatment of minor cuts and abrasions. Discontinue use and get medical aid if redness, irritation or infection develops. In case of deep or puncture wounds consult a physician.

Inactive Ingredients: Water

PACKAGE LABEL

baklabel.jpg